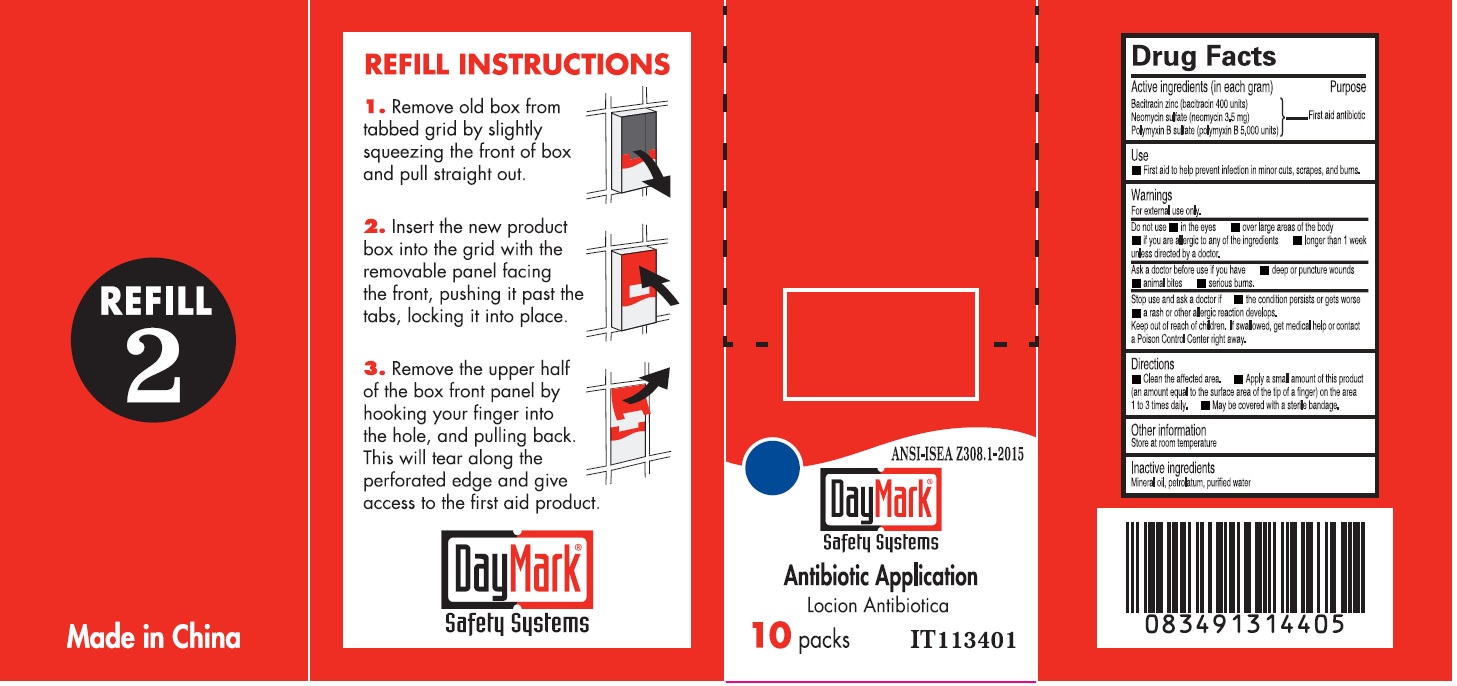 DRUG LABEL: Antibiotic Application
NDC: 49687-0013 | Form: OINTMENT
Manufacturer: CMC Group, Inc.
Category: otc | Type: HUMAN OTC DRUG LABEL
Date: 20250113

ACTIVE INGREDIENTS: BACITRACIN ZINC 400 [iU]/1 g; NEOMYCIN SULFATE 3.5 mg/1 g; POLYMYXIN B SULFATE 5000 [iU]/1 g
INACTIVE INGREDIENTS: MINERAL OIL; PETROLATUM; WATER

Antibiotic Application

Active ingredients (in each gram)

Bacitracin zinc (bacitracin 400 units)

Neomycin sulfate (neomycin 3.5mg)

Polymyxin B sulfate (polymyxin B 5,000 units)

Purpose

First aid antibiotic

Use

- First aid to help prevent infection in minor cuts, scrapes, and burns.

Warnings

For external use only.

Do not use

• in the eyes • over large areas of the body • if you are allergic to any of the ingredient • longer than 1 week unless directed by a doctor.

Ask a doctor before use if you have

• deep or punture wounds • animal bites • serious burns.

Stop use and ask a doctor if

• the condition persists or gets worse • a rash or other allergic reaction develops.

Keep out of reach of children.

If swallowed, get medical help or contact a Poison Control Center right away.

Directions

• Clean the affected area. • Apply a small amount of this product (an amount equal to the surface area of the tip of a finger) on the area 1 to 3 times daily. • May be covered with a sterile bandage.

Other information

Store at room temperature

Inactive ingredients

Mineral oil, petrolatum, purified water